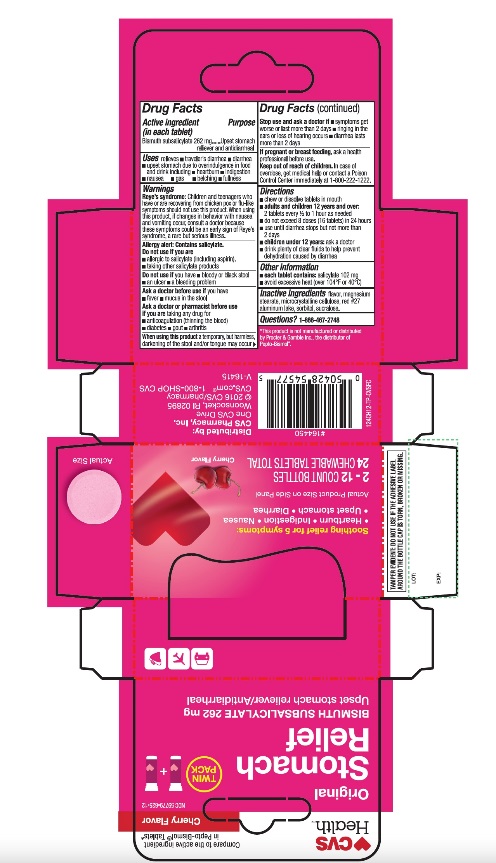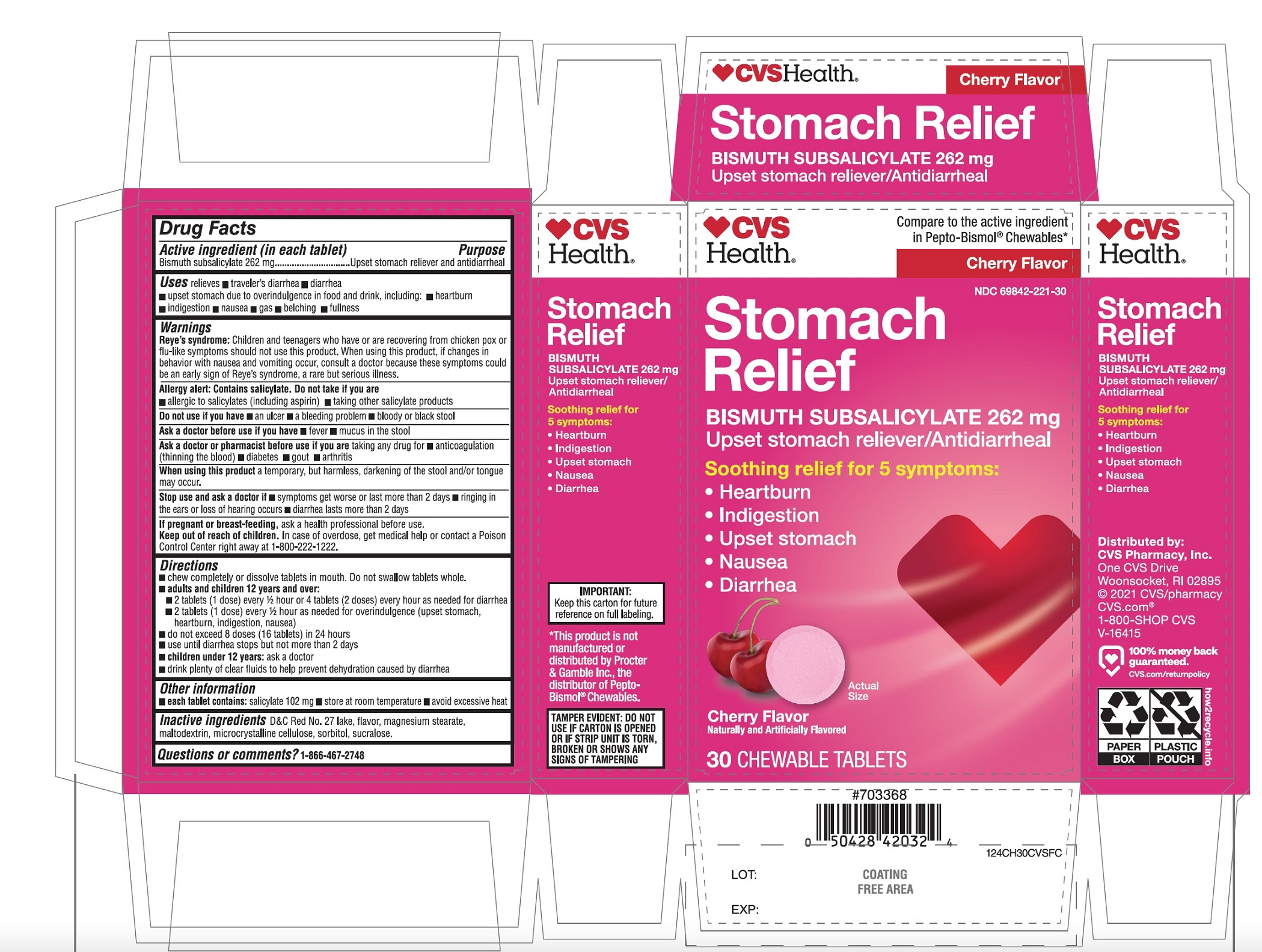 DRUG LABEL: CVS Health Stomach relief

NDC: 69842-221 | Form: TABLET, CHEWABLE
Manufacturer: CVS PHARMACY,INC.
Category: otc | Type: HUMAN OTC DRUG LABEL
Date: 20251208

ACTIVE INGREDIENTS: BISMUTH SUBSALICYLATE 262 mg/1 1
INACTIVE INGREDIENTS: D&C RED NO. 27; MAGNESIUM STEARATE; MALTODEXTRIN; MICROCRYSTALLINE CELLULOSE; SORBITOL; SUCRALOSE

CVS Health™Stomach Relief Bismuth Subsalicylate 24 Chewable Tablets

Active ingredient (in each tablet)

Bismuth subsalicylate 262 mg

Purpose

Upset stomach reliever and anti-diarrheal

Uses

relieves:

- travelers’ diarrhea
- diarrhea
- upset stomach due to overindulgence in food and drink, including:
- heartburn
- indigestion
- nausea
- gas
- belching
- fullness

Warnings

Reye's syndrome:Children and teenagers who have or are recovering from chicken pox or flu-like symptoms should not use this product. When using this product, if changes in behavior with nausea and vomiting occur, consult a doctor because these symptoms could be an early sign of Reye's syndrome, a rare but serious illness.

Allergy alert: Contains salicylate. Do not take if you are

- allergic to salicylates (including aspirin)
- taking other salicylate products

Do not use if you have

- an ulcer
- a bleeding problem
- bloody or black stool

Ask a doctor before use if you have

- fever
- mucus in the stool

Ask a doctor or pharmacist before use if you aretaking any drug for

- anticoagulation (thinning of the blood)
- diabetes
- gout
- arthritis

When using this product

a temporary, but harmless, darkening of the stool and/or tongue may occur.

Stop use and ask a doctor if

- symptoms get worse or last more than 2 days
- ringing in the ears or loss of hearing occurs
- diarrhea lasts more than 2 days

If pregnant or breast-feeding,ask a health professional before use .

Keep Out of Reach of Children

In case of overdose, get medical help or contact a Poison Control Center immediately at 1-800-222-1222

Directions

- chew completely or dissolve tablets in mouth.
- adults and children 12 years and older:2 tablets every 1/2 to 1 hour as needed
- do not exceed 8 doses (16 tablets) in 24 hours
- use until diarrhea stops but not more than 2 days
- children under 12 years:ask a doctor
- drink plenty clear fluids to help prevent dehydration caused by diarrhea.

Other information

- each tablet contains: salicylate 102 mg
- store at room temperature
- avoid excessive heat
- keep this carton for future reference on full labeling

TAMPER EVIDENT: DO NOT USE IF THE ADHESIVE LABELS AROUND THE BOTTLE CAP IS TORN, BROKEN OR MISSING.

Inactive ingredients

D&C Red No. 27 lake, flavor, magnesium stearate, maltodextrin, microcrystalline cellulose, sorbitol, sucralose.

Questions?

1-866-467-2748

Principal Display

CVS Health™

NDC# 69842-221-12

Compare To the active ingredient in Pepto-Bismol®Tablets*

Cherry Flavor

Original TWIN PACK

Stomach relief

BISMUTH SUBSALICYLATE 262 mg

Upset stomach reliever/Antidiarrheal

Soothing relief for 5 symptoms:

- Heartburn
- Indigestion Nausea
- Upset stomach
- Diarrhea

2-12 COUNT BOTTLES

24 CHEWABLE TABLETS TOTAL

Cherry Flavor

Distributed by:

CVS Pharmacy, Inc.

One CVS Drive

Woonsocket, RI 02895

© 2016 CVS/pharmacy

CVS.com 1-800-SHOP CVS

V-16415

*This product is not manufactured or distributed by The Procter & Gamble Co., the distributor of Pepto-Bismol®.

Package Label for 24 Chewable tablets